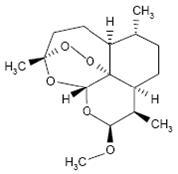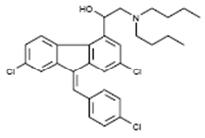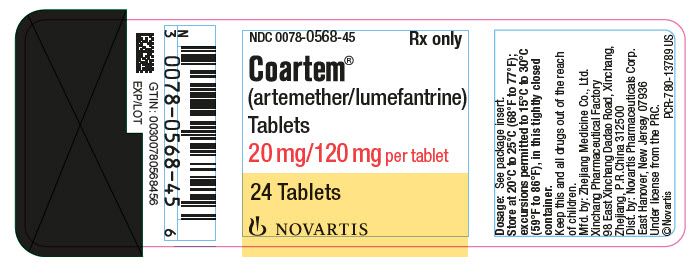 DRUG LABEL: COARTEM
NDC: 0078-0568 | Form: TABLET
Manufacturer: Novartis Pharmaceuticals Corporation
Category: prescription | Type: HUMAN PRESCRIPTION DRUG LABEL
Date: 20250617

ACTIVE INGREDIENTS: ARTEMETHER 20 mg/1 1; LUMEFANTRINE 120 mg/1 1
INACTIVE INGREDIENTS: SILICON DIOXIDE; CROSCARMELLOSE SODIUM; HYPROMELLOSES; MAGNESIUM STEARATE; CELLULOSE, MICROCRYSTALLINE; POLYSORBATE 80; WATER

HIGHLIGHTS OF PRESCRIBING INFORMATION

These highlights do not include all the information needed to use COARTEM Tablets safely and effectively. See full prescribing information for COARTEM Tablets.
COARTEM® (artemether and lumefantrine) tablets, for oral use
Initial U.S. Approval: 2009

1 INDICATIONS AND USAGE

- Coartem Tablets are a combination of artemether and lumefantrine, both antimalarials, indicated for treatment of acute, uncomplicated malaria infections due to Plasmodium falciparum (P. falciparum) in patients 2 months of age and older with a bodyweight of 5 kg and above. (1)
- Coartem Tablets have been shown to be effective in geographical regions where resistance to chloroquine has been reported. (1)

Limitations of Use: (1)

- Coartem Tablets are not approved for patients with severe or complicated P. falciparum malaria.
- Coartem Tablets are not approved for the prevention of malaria.

2 DOSAGE AND ADMINISTRATION

- Coartem Tablets should be taken with food. (2.1, 5.2)
- Tablets may be crushed and mixed with 1 to 2 teaspoons of water immediately prior to administration to patients, including children. (2.1)
- Coartem Tablets should be administered over 3 days for a total of 6 doses: an initial dose, second dose after 8 hours, and then twice-daily (morning and evening) for the following 2 days. (2.2, 2.3)
- The adult dosage for patients with bodyweight of 35 kg and above is 4 tablets per dose for a total of 6 doses. (2.2)
- The number of tablets per dose for children is determined by bodyweight, as shown in the chart below. (2.3)

Tablets per dose by bodyweight; total of 6 doses over 3 days
5 to < 15 kg | 1 tablet
15 to < 25 kg | 2 tablets
25 to < 35 kg | 3 tablets
35 kg and over | 4 tablets

3 DOSAGE FORMS AND STRENGTHS

Tablets are scored and contain 20 mg artemether and 120 mg lumefantrine. (3)

4 CONTRAINDICATIONS

- Known hypersensitivity to artemether, lumefantrine, or to any of the excipients. (4)
- Coadministration of strong inducers of CYP3A4 such as rifampin, carbamazepine, phenytoin, and St. John’s wort with Coartem Tablets. (4, 7.1, 12.3)

5 WARNINGS AND PRECAUTIONS

- Avoid use in patients with known QT prolongation, those with hypokalemia or hypomagnesemia, and those taking other drugs that prolong the QT interval. (5.1, 12.6)
- Halofantrine and Coartem Tablets should not be administered within one month of each other due to potential additive effects on the QT interval. (5.1, 5.2, 12.3)
- Antimalarials should not be given concomitantly, unless there is no other treatment option, due to limited safety data. (5.2)
- QT prolonging drugs, including quinine and quinidine, should be used cautiously following Coartem Tablets. (5.1, 5.2, 7.7, 12.3)
- Substrates, inhibitors, or inducers of CYP3A4, including antiretroviral medications, should be used cautiously with Coartem Tablets, due to a potential loss of efficacy of the concomitant drug or additive QT prolongation. (5.3, 7.2, 7.3)

6 ADVERSE REACTIONS

The most common adverse reactions in adults (greater than 30%) are headache, anorexia, dizziness, asthenia, arthralgia, and myalgia. The most common adverse reactions in children (greater than 12%) are pyrexia, cough, vomiting, anorexia, and headache. (6.1)

To report SUSPECTED ADVERSE REACTIONS, contact Novartis Pharmaceuticals Corporation at 1-888-669-6682 or FDA at 1-800-FDA-1088 or www.fda.gov/medwatch.

7 DRUG INTERACTIONS

- CYP3A4 Inducers: Potential for loss of antimalarial efficacy. (4, 5.3, 7.1, 12.3)
- CYP3A4 Inhibitors: Use cautiously due to potential for QT prolongation. (5.3, 7.2, 12.3)
- Antiretrovirals: Use cautiously due to potential for QT prolongation, loss of antiviral efficacy, or loss of antimalarial efficacy of Coartem Tablets. (5.3, 7.3, 12.3)
- Mefloquine: If used immediately before treatment, monitor for decreased efficacy of Coartem Tablets and encourage food consumption. (2.1, 7.4, 12.3)
- Hormonal Contraceptives: Effectiveness may be reduced; use an additional method of birth control. (5.3, 7.5, 12.3)
- CYP2D6 Substrates: Monitor for adverse reactions and potential QT prolongation. (5.1, 5.4, 7.6)

FULL PRESCRIBING INFORMATION

1 INDICATIONS AND USAGE

Coartem Tablets are indicated for treatment of acute, uncomplicated malaria infections due to Plasmodium falciparum (P. falciparum) in patients 2 months of age and older with a bodyweight of 5 kg and above. Coartem Tablets have been shown to be effective in geographical regions where resistance to chloroquine has been reported [see Clinical Studies (14.1)].

Limitations of Use:

- Coartem Tablets are not approved for patients with severe or complicated P. falciparum malaria.
- Coartem Tablets are not approved for the prevention of malaria.

2 DOSAGE AND ADMINISTRATION

2.1 Administration Instructions

Coartem Tablets should be taken with food. Patients with acute malaria are frequently averse to food. Patients should be encouraged to resume normal eating as soon as food can be tolerated since this improves absorption of artemether and lumefantrine.

For patients who are unable to swallow the tablets such as infants and children, Coartem Tablets may be crushed and mixed with a small amount of water (1 to 2 teaspoons) in a clean container for administration immediately prior to use. The container can be rinsed with more water and the contents swallowed by the patient. The crushed tablet preparation should be followed whenever possible by food/drink (e.g., milk, formula, pudding, broth, and porridge).

In the event of vomiting within 1 to 2 hours after administration, a repeat dose should be taken. If the repeat dose is vomited, the patient should be given an alternative antimalarial for treatment.

2.2 Dosage in Adult Patients (greater than 16 years of age)

A 3-day treatment schedule with a total of 6 doses is recommended for adult patients with a bodyweight of 35 kg and above:

Four tablets as a single initial dose, 4 tablets again after 8 hours, and then 4 tablets twice-daily (morning and evening) for the following 2 days (total course of 24 tablets).

For patients weighing less than 35 kg, [see Dosage and Administration (2.3)].

2.3 Dosage in Pediatric Patients

A 3-day treatment schedule with a total of 6 doses is recommended as below:

5 kg to less than 15 kg bodyweight: One tablet as an initial dose, 1 tablet again after 8 hours, and then 1 tablet twice daily (morning and evening) for the following 2 days (total course of 6 tablets).

15 kg to less than 25 kg bodyweight: Two tablets as an initial dose, 2 tablets again after 8 hours, and then 2 tablets twice daily (morning and evening) for the following 2 days (total course of 12 tablets).

25 kg to less than 35 kg bodyweight: Three tablets as an initial dose, 3 tablets again after 8 hours, and then 3 tablets twice daily (morning and evening) for the following 2 days (total course of 18 tablets).

35 kg bodyweight and above: Four tablets as a single initial dose, 4 tablets again after 8 hours, and then 4 tablets twice daily (morning and evening) for the following 2 days (total course of 24 tablets).

2.4 Dosage in Patients With Hepatic or Renal Impairment

No specific pharmacokinetic studies have been carried out in patients with hepatic or renal impairment. Most patients with acute malaria present with some degree of related hepatic and/or renal impairment. In clinical studies, the adverse event profile did not differ in patients with mild or moderate hepatic impairment compared to patients with normal hepatic function. No specific dose adjustments are needed for patients with mild or moderate hepatic impairment.

In clinical studies, the adverse event profile did not differ in patients with mild or moderate renal impairment compared to patients with normal renal function. There were few patients with severe renal impairment in clinical studies. There is no significant renal excretion of lumefantrine, artemether, and dihydroartemisinin (DHA) in healthy volunteers and while clinical experience in this population is limited, no dose adjustment is recommended.

Caution should be exercised when administering Coartem Tablets in patients with severe hepatic or renal impairment [see Warnings and Precautions (5.6)].

3 DOSAGE FORMS AND STRENGTHS

Coartem Tablets contain 20 mg of artemether and 120 mg of lumefantrine. Coartem Tablets are supplied as yellow, round, flat tablets with beveled edges and scored on one side. Tablets are imprinted with “N/C” on one side and “CG” on the other side.

4 CONTRAINDICATIONS

Hypersensitivity

Known hypersensitivity to artemether, lumefantrine, or to any of the excipients of Coartem Tablets [see Adverse Reactions (6.2)].

Strong CYP3A4 Inducers

Coadministration of strong inducers of CYP3A4 such as rifampin, carbamazepine, phenytoin, and St. John’s wort with Coartem Tablets can result in decreased concentrations of artemether and/or lumefantrine and loss of antimalarial efficacy [see Warnings and Precautions (5.3), Drug Interactions (7.1), and Clinical Pharmacology (12.3)].

5 WARNINGS AND PRECAUTIONS

5.1 Prolongation of the QT Interval

Some antimalarials (e.g., halofantrine, quinine, quinidine) including Coartem Tablets have been associated with prolongation of the QT interval on the electrocardiogram (ECG).

Coartem Tablets should be avoided in patients:

- With congenital prolongation of the QT interval (e.g., long QT syndrome) or any other clinical condition known to prolong the QTc interval such as patients with a history of symptomatic cardiac arrhythmias, with clinically relevant bradycardia or with severe cardiac disease.
- With a family history of congenital prolongation of the QT interval or sudden death.
- With known disturbances of electrolyte balance, e.g., hypokalemia or hypomagnesemia.
- Receiving other medications that prolong the QT interval, such as Class IA (quinidine, procainamide, disopyramide), or Class III (amiodarone, sotalol) antiarrhythmic agents; antipsychotics (pimozide, ziprasidone); antidepressants; certain antibiotics (macrolide antibiotics, fluoroquinolone antibiotics, imidazole, and triazole antifungal agents) [see Clinical Pharmacology (12.6)].
- Receiving medications that are metabolized by the cytochrome enzyme CYP2D6, which also have cardiac effects (e.g., flecainide, imipramine, amitriptyline, clomipramine) [see Warnings and Precautions (5.4), Drug Interactions (7.6), and Clinical Pharmacology (12.3)].

5.2 Use of QT Prolonging Drugs and Other Antimalarials

Halofantrine and Coartem Tablets should not be administered within 1 month of each other due to the long elimination half-life of lumefantrine (3 to 6 days) and potential additive effects on the QT interval [see Warnings and Precautions (5.1) and Clinical Pharmacology (12.3)].

Antimalarials should not be given concomitantly with Coartem Tablets, unless there is no other treatment option, due to limited safety data.

Drugs that prolong the QT interval, including antimalarials such as quinine and quinidine, should be used cautiously following Coartem Tablets, due to the long elimination half-life of lumefantrine (3 to 6 days) and the potential for additive effects on the QT interval; ECG monitoring is advised if use of drugs that prolong the QT interval is medically required [see Warnings and Precautions (5.1), Drug Interactions (7.7), and Clinical Pharmacology (12.3)].

If mefloquine is administered immediately prior to Coartem Tablets, there may be a decreased exposure to lumefantrine, possibly due to a mefloquine-induced decrease in bile production. Therefore, patients should be monitored for decreased efficacy and food consumption should be encouraged while taking Coartem Tablets [see Dosage and Administration (2.1), Drug Interactions (7.4), and Clinical Pharmacology (12.3)].

5.3 Drug Interactions With CYP3A4

When Coartem Tablets are coadministered with substrates of CYP3A4, it may result in decreased concentrations of the substrate and potential loss of substrate efficacy. When Coartem Tablets are coadministered with an inhibitor of CYP3A4, including grapefruit juice, it may result in increased concentrations of artemether and/or lumefantrine and potentiate QT prolongation. When Coartem Tablets are coadministered with inducers of CYP3A4, it may result in decreased concentrations of artemether and/or lumefantrine and loss of antimalarial efficacy [see Contraindications (4) and Drug Interactions (7)].

Drugs that have a mixed effect on CYP3A4, especially antiretroviral drugs such as HIV protease inhibitors and non-nucleoside reverse transcriptase inhibitors, and those that have an effect on the QT interval should be used with caution in patients taking Coartem Tablets [see Drug Interactions (7.3, 7.7)].

Coartem Tablets may reduce the effectiveness of hormonal contraceptives. Therefore, patients using hormonal contraceptives should be advised to use an alternative non-hormonal contraceptive method or add a barrier method of contraception during treatment with Coartem [see Drug Interactions (7.5)].

5.4 Drug Interactions With CYP2D6

Administration of Coartem Tablets with drugs that are metabolized by CYP2D6 may significantly increase plasma concentrations of the coadministered drug and increase the risk of adverse effects. Many of the drugs metabolized by CYP2D6 can prolong the QT interval and should not be administered with Coartem Tablets due to the potential additive effect on the QT interval (e.g., flecainide, imipramine, amitriptyline, clomipramine) [see Warnings and Precautions (5.1), Drug Interactions (7.6), and Clinical Pharmacology (12.3)].

5.5 Recrudescence

Food enhances absorption of artemether and lumefantrine following administration of Coartem Tablets. Patients who remain averse to food during treatment should be closely monitored as the risk of recrudescence may be greater [see Dosage and Administration (2.1)].

In the event of recrudescent P. falciparum infection after treatment with Coartem Tablets, patients should be treated with a different antimalarial drug.

5.6 Hepatic and Renal Impairment

Coartem Tablets have not been studied for efficacy and safety in patients with severe hepatic and/or renal impairment [see Dosage and Administration (2.4)].

5.7 Plasmodium vivax Infection

Coartem Tablets have been shown in limited data (43 patients) to be effective in treating the erythrocytic stage of P. vivax infection. However, relapsing malaria caused by P. vivax requires additional treatment with other antimalarial agents to achieve radical cure i.e., eradicate any hypnozoites forms that may remain dormant in the liver.

6 ADVERSE REACTIONS

The following serious and otherwise important adverse reactions are discussed in greater detail in other sections of labeling:

- Hypersensitivity Reactions [see Contraindications (4)]
- Prolongation of the QT Interval [see Warnings and Precautions (5.1)]
- Use of QT Prolonging Drugs and Other Antimalarials [see Warnings and Precautions (5.2)]
- Drug Interactions with CYP3A4 [see Warnings and Precautions (5.3)]
- Drug Interactions with CYP2D6 [see Warnings and Precautions (5.4)]

6.1 Clinical Trials Experience

Because clinical trials are conducted under widely varying conditions, adverse reaction rates observed in the clinical trials of a drug cannot be directly compared to rates in the clinical trials of another drug and may not reflect the rate observed in practice.

The data described below reflect exposure to a 6-dose regimen of Coartem Tablets in 1979 patients including 647 adults (older than 16 years) and 1332 children (16 years and younger). For the 6-dose regimen, Coartem Tablets was studied in active-controlled (366 patients) and noncontrolled, open-label trials (1613 patients). The 6-dose Coartem Tablets population was patients with malaria between ages 2 months and 71 years: 67% (1332) were 16 years and younger and 33% (647) were older than 16 years. Males represented 73% and 53% of the adult and pediatric populations, respectively. The majority of adult patients were enrolled in studies in Thailand, while the majority of pediatric patients were enrolled in Africa.

Tables 1 and 2 show the most frequently reported adverse reactions (greater than or equal to 3%) in adults and children respectively who received the 6-dose regimen of Coartem Tablets. Adverse reactions collected in clinical trials included signs and symptoms at baseline, but only treatment emergent adverse events, defined as events that appeared or worsened after the start of treatment, are presented below. In adults, the most frequently reported adverse reactions were headache, anorexia, dizziness, and asthenia. In children, the adverse reactions were pyrexia, cough, vomiting, anorexia, and headache. Most adverse reactions were mild, did not lead to discontinuation of study medication, and resolved.

In limited comparative studies, the adverse reaction profile of Coartem Tablets appeared similar to that of another antimalarial regimen.

Discontinuation of Coartem Tablets due to adverse drug reactions occurred in 1.1% of patients treated with the 6-dose regimen overall: 0.2% (1/647) in adults and 1.6% (21/1332) in children.

Table 1: Adverse Reactions Occurring in 3% or More of Adult Patients Treated in Clinical Trials With the 6-dose Regimen of Coartem Tablets
System Organ Class | Preferred Term | Adults* N = 647 (%)
Nervous system disorders | Headache | 360 (56)
 | Dizziness | 253 (39)
Metabolism and nutrition disorders | Anorexia | 260 (40)
General disorders and administration site conditions | Asthenia | 243 (38)
 | Pyrexia | 159 (25)
 | Chills | 147 (23)
 | Fatigue | 111 (17)
 | Malaise | 20 (3)
Musculoskeletal and connective tissue disorders | Arthralgia | 219 (34)
 | Myalgia | 206 (32)
Gastrointestinal disorders | Nausea | 169 (26)
 | Vomiting | 113 (17)
 | Abdominal pain | 112 (17)
 | Diarrhea | 46 (7)
Psychiatric disorders | Sleep disorder | 144 (22)
 | Insomnia | 32 (5)
Cardiac disorders | Palpitations | 115 (18)
Hepatobiliary disorders | Hepatomegaly | 59 (9)
Blood and lymphatic system disorders | Splenomegaly | 57 (9)
 | Anemia | 23 (4)
Respiratory, thoracic and mediastinal disorders | Cough | 37 (6)
Skin and subcutaneous tissue disorders | Pruritus | 24 (4)
 | Rash | 21 (3)
Ear and labyrinth disorders | Vertigo | 21 (3)
Infections and infestations | Malaria | 18 (3)
 | Nasopharyngitis | 17 (3)
*Adult patients defined as greater than 16 years of age.

Table 2: Adverse Reactions Occurring in 3% or More of Pediatric Patients Treated in Clinical Trials With the 6-dose Regimen of Coartem Tablets
System Organ Class | Preferred Term | Children* N = 1332 (%)
General disorders and administration site conditions | Pyrexia | 381 (29)
 | Chills | 72 (5)
 | Asthenia | 63 (5)
 | Fatigue | 46 (3)
Respiratory, thoracic and mediastinal disorders | Cough | 302 (23)
Gastrointestinal disorders | Vomiting | 242 (18)
 | Abdominal pain | 112 (8)
 | Diarrhea | 100 (8)
 | Nausea | 61 (5)
Infections and infestations | Plasmodium falciparum infection | 224 (17)
 | Rhinitis | 51 (4)
Metabolism and nutrition disorders | Anorexia | 175 (13)
Nervous system disorders | Headache | 168 (13)
 | Dizziness | 56 (4)
Blood and lymphatic system disorders | Splenomegaly | 124 (9)
 | Anemia | 115 (9)
Hepatobiliary disorders | Hepatomegaly | 75 (6)
Investigations | Aspartate aminotransferase increased | 51 (4)
Musculoskeletal and connective tissue disorders | Arthralgia | 39 (3)
 | Myalgia | 39 (3)
Skin and subcutaneous tissue disorders | Rash | 38 (3)
*Children defined as patients less than or equal to 16 years of age.

Clinically significant adverse reactions reported in adults and/or children treated with the 6-dose regimen of Coartem Tablets, which occurred in clinical studies at less than 3% regardless of causality are listed below:

Blood and Lymphatic System Disorders: eosinophilia

Ear and Labyrinth Disorders: tinnitus

Eye Disorders: conjunctivitis

Gastrointestinal Disorders: constipation, dyspepsia, dysphagia, peptic ulcer

General Disorders: gait disturbance

Infections and Infestations: abscess, acrodermatitis, bronchitis, ear infection, gastroenteritis, helminthic infection, hook-worm infection, impetigo, influenza, lower respiratory tract infection, malaria, nasopharyngitis, oral herpes, pneumonia, respiratory tract infection, subcutaneous abscess, upper respiratory tract infection, urinary tract infection

Investigations: alanine aminotransferase increased, aspartate aminotransferase increased, hematocrit decreased, lymphocyte morphology abnormal, platelet count decreased, platelet count increased, white blood cell count decreased, white blood cell count increased

Metabolism and Nutrition Disorders: hypokalemia

Musculoskeletal and Connective Tissue Disorders: back pain

Nervous System Disorders: ataxia, clonus, fine motor delay, hyperreflexia, hypoesthesia, nystagmus, tremor

Psychiatric Disorders: agitation, mood swings

Renal and Urinary Disorders: hematuria, proteinuria

Respiratory, Thoracic and Mediastinal Disorders: asthma, pharyngo-laryngeal pain

Skin and Subcutaneous Tissue Disorders: urticaria

6.2 Postmarketing Experience

The following adverse reactions have been identified during postapproval use of Coartem Tablets. Because these events are reported voluntarily from a population of uncertain size, it is not always possible to reliably estimate their frequency or establish a causal relationship to drug exposure.

- Hypersensitivity Reactions: anaphylaxis, urticaria, angioedema, and serious skin reactions (bullous eruption) have been reported.
- Blood and Lymphatic System Disorders: Cases of delayed hemolytic anemia have been reported following treatment with artemether-lumefantrine, mostly when used for treatment of severe malaria in patients initially treated with IV/parenteral artesunate. Coartem Tablets should not be used to treat severe malaria as it is not an approved indication.

7 DRUG INTERACTIONS

7.1 Rifampin

Oral administration of rifampin, a strong CYP3A4 inducer, with Coartem Tablets resulted in significant decreases in exposure to artemether, DHA (metabolite of artemether), and lumefantrine by 89%, 85%, and 68%, respectively, when compared to exposure values after Coartem Tablets alone. Concomitant use of strong inducers of CYP3A4 such as rifampin, carbamazepine, phenytoin, and St. John’s wort is contraindicated with Coartem Tablets [see Contraindications (4) and Clinical Pharmacology (12.3)].

7.2 Ketoconazole

Concurrent oral administration of ketoconazole, a potent CYP3A4 inhibitor, with a single dose of Coartem Tablets resulted in a moderate increase in exposure to artemether, DHA, and lumefantrine in a study of 15 healthy subjects. No dose adjustment of Coartem Tablets is necessary when administered with ketoconazole or other potent CYP3A4 inhibitors. However, due to the potential for increased concentrations of lumefantrine which could lead to QT prolongation, Coartem Tablets should be used cautiously with drugs that inhibit CYP3A4 [see Warnings and Precautions (5.1, 5.3) and Clinical Pharmacology (12.3)].

7.3 Antiretroviral Drugs

Both artemether and lumefantrine are metabolized by CYP3A4. Antiretroviral drugs, such as protease inhibitors and non-nucleoside reverse transcriptase inhibitors, are known to have variable patterns of inhibition, induction or competition for CYP3A4. Therefore, the effects of antiretroviral drugs on the exposure to artemether, DHA, and lumefantrine are also variable [see Clinical Pharmacology (12.3)]. Coartem Tablets should be used cautiously in patients on antiretroviral drugs because decreased artemether, DHA, and/or lumefantrine concentrations may result in a decrease of antimalarial efficacy of Coartem Tablets, and increased lumefantrine concentrations may cause QT prolongation [see Warnings and Precautions (5.3)].

7.4 Prior Use of Mefloquine

Administration of 3 doses of mefloquine followed 12 hours later by a 6-dose regimen of Coartem Tablets in 14 healthy volunteers demonstrated no effect of mefloquine on plasma concentrations of artemether or the artemether/DHA ratio. However, exposure to lumefantrine was reduced, possibly due to lower absorption secondary to a mefloquine-induced decrease in bile production. Patients should be monitored for decreased efficacy and food consumption should be encouraged with administration of Coartem Tablets [see Warnings and Precautions (5.2) and Clinical Pharmacology (12.3)].

7.5 Hormonal Contraceptives

In vitro, the metabolism of ethinyl estradiol and levonorgestrel was not induced by artemether, DHA, or lumefantrine. However, artemether has been reported to weakly induce, in humans, the activity of CYP2C19, CYP2B6, and CYP3A4. Therefore, Coartem Tablets may potentially reduce the effectiveness of hormonal contraceptives. Patients using hormonal contraception should be advised to use an alternative non-hormonal contraceptive method or add a barrier method of contraception during treatment with Coartem [see Warnings and Precautions (5.3), Use in Specific Populations (8.3) and Clinical Pharmacology (12.3)].

7.6 CYP2D6 Substrates

Lumefantrine inhibits CYP2D6 in vitro. Administration of Coartem Tablets with drugs that are metabolized by CYP2D6 may significantly increase plasma concentrations of the coadministered drug and increase the risk of adverse effects. Many of the drugs metabolized by CYP2D6 can prolong the QT interval and should not be administered with Coartem Tablets due to the potential additive effect on the QT interval (e.g., flecainide, imipramine, amitriptyline, clomipramine) [see Warnings and Precautions (5.1, 5.4) and Clinical Pharmacology (12.3)].

7.7 Sequential Use of Quinine

A single dose of intravenous quinine (10 mg/kg bodyweight) concurrent with the final dose of a 6-dose regimen of Coartem Tablets demonstrated no effect of intravenous quinine on the systemic exposure of DHA or lumefantrine. Quinine exposure was also not altered. Exposure to artemether was decreased. This decrease in artemether exposure is not thought to be clinically significant. However, quinine and other drugs that prolong the QT interval should be used cautiously following treatment with Coartem Tablets due to the long elimination half-life of lumefantrine and the potential for additive QT effects; ECG monitoring is advised if use of drugs that prolong the QT interval is medically required [see Warnings and Precautions (5.2) and Clinical Pharmacology (12.3)].

7.8 Interaction With Drugs That are Known to Prolong the QT Interval

Coartem Tablets are to be used with caution when coadministered with drugs that may cause prolonged QT interval such as antiarrhythmics of Classes IA and III, neuroleptics and antidepressant agents, certain antibiotics including some agents of the following classes: macrolides, fluoroquinolones, imidazole, and triazole antifungal agents [see Warnings and Precautions (5.1, 5.2)].

8 USE IN SPECIFIC POPULATIONS

8.1 Pregnancy

Risk Summary

Published data from clinical studies and pharmacovigilance data have not established an association with artemether/lumefantrine use during pregnancy and major birth defects, miscarriage, or adverse maternal or fetal outcomes (see Data).

The estimated background risk of major birth defects and miscarriage for the indicated population is unknown. All pregnancies have a background risk of birth defect, loss, or other adverse outcomes. In the U.S. general population, the estimated background risk of major birth defects and miscarriage in clinically recognized pregnancies is 2% to 4% and 15% to 20%, respectively.

Clinical Considerations

Disease-Associated Maternal and/or Embryo/Fetal Risk

Malaria during and after pregnancy increases the risk for adverse pregnancy and neonatal outcomes, including maternal anemia, severe malaria, spontaneous abortion, stillbirths, preterm delivery, low birth weight, intrauterine growth restriction, congenital malaria, and maternal and neonatal mortality.

Data

Human Data

While available studies cannot definitively establish the absence of risk, a meta-analysis of observational studies including over 500 artemether-lumefantrine exposed women in their first trimester of pregnancy, data from observational, and open label studies including more than 1200 pregnant women in their second- or third trimester exposed to artemether-lumefantrine compared to other antimalarials, and pharmacovigilance data have not demonstrated an increase in major birth defects, miscarriage, or adverse maternal or fetal outcomes. Published epidemiologic studies have important methodological limitations which hinder interpretation of data, including inability to control for confounders, such as underlying maternal disease, and maternal use of concomitant medications and missing information on the dose and duration of use.

Animal Data

Pregnant rats dosed orally during the period of organogenesis [gestational days (GD) 7 through 17] at 50 mg/kg/day artemether-lumefantrine combination (corresponding to 7 mg/kg/day artemether or higher, a dose of less than half the maximum recommended human dose (MRHD) of 1120 mg artemether-lumefantrine per day (based on body surface area (BSA) comparisons), showed increases in fetal loss, early resorptions, and postimplantation loss. No adverse effects were observed in animals dosed at 25 mg/kg/day artemether-lumefantrine (corresponding to 3.6 mg/kg/day of artemether), about one-third the MRHD (based on BSA comparison). Similarly, oral dosing in pregnant rabbits during organogenesis (GD 7 through GD 19) at 175 mg/kg/day, (corresponding to 25 mg/kg/day artemether) about 3 times the MRHD (based on BSA comparisons) resulted in abortions, preimplantation loss, post implantation loss and decreases in the number of live fetuses. No adverse reproductive effects were detected in rabbits at 105 mg/kg/day artemether-lumefantrine (corresponding to 15 mg/kg/day artemether), about 2 times the MRHD. Artemether and other artemisinins are associated with maternal toxicity and embryotoxicity and malformations in animals at clinically relevant exposures; however, lumefantrine doses as high as 1000 mg/kg/day, showed no evidence to suggest maternal, embryo- or fetotoxicity or teratogenicity in rats and rabbits. The relevance of the findings from the animal reproductive studies to human risk is unclear.

8.2 Lactation

Risk Summary

There are no data on the presence of artemether or lumefantrine in human milk, the effects on the breastfed infant or the effects on milk production. Artemether and lumefantrine are transferred into rat milk. When a drug is transferred into animal milk, it is likely that the drug will also be transferred into human milk. The developmental and health benefits of breastfeeding should be considered along with the mother’s clinical need for Coartem and any potential adverse effects on the breastfed infant from Coartem or from the underlying maternal condition.

8.3 Females and Males of Reproductive Potential

Contraception

Use of Coartem may reduce the efficacy of hormonal contraceptives. Advise patients using hormonal contraceptives to use an alternative non-hormonal contraceptive method or add a barrier method of contraception during treatment with Coartem [see Drug Interactions (7.5)].

Infertility

In animal fertility studies, administration of repeated doses of artemether-lumefantrine combination to female rats (for 2 to 4 weeks) resulted in pregnancy rates that were reduced by one half. In male rats dosed for approximately 3 months with artemether-lumefantrine combination, abnormal sperm cells, decreased sperm motility, and increased testes weight were observed [see Nonclinical Toxicology (13.1)].

8.4 Pediatric Use

The safety and effectiveness of Coartem Tablets have been established in pediatric patients aged 2 months and older with a bodyweight of 5 kg and above for the treatment of acute, uncomplicated malaria [see Clinical Studies (14.1)]. The safety and effectiveness of Coartem Tablets have not been established in pediatric patients younger than 2 months old or who weigh less than 5 kg. Pediatric patients from non-endemic countries were not included in clinical trials.

8.5 Geriatric Use

Clinical studies of Coartem Tablets did not include sufficient numbers of subjects aged 65 years and over to determine whether they respond differently from younger subjects. In general, the greater frequency of decreased hepatic, renal, or cardiac function, and of concomitant disease or other drug therapy in elderly patients should be considered when prescribing Coartem Tablets.

8.6 Hepatic and Renal Impairment

No specific pharmacokinetic studies have been performed in patients with either hepatic or renal impairment. Coartem Tablets have not been studied for efficacy and safety in patients with severe hepatic and/or renal impairment. Based on the pharmacokinetic data in 16 healthy subjects showing no or insignificant renal excretion of lumefantrine, artemether, and DHA, no dose adjustment for the use of Coartem Tablets in patients with renal impairment is advised. No dosage adjustment is necessary in patients with mild-to-moderate hepatic impairment [see Dosage and Administration (2.4) and Warnings and Precautions (5.6)].

10 OVERDOSAGE

There is no information on overdoses of Coartem Tablets higher than the doses recommended for treatment.

In cases of suspected overdosage, symptomatic and supportive therapy, which would include ECG and blood electrolyte monitoring, should be given as appropriate.

11 DESCRIPTION

Coartem Tablets contain a fixed combination of 2 antimalarial active ingredients, artemether, an artemisinin derivative, and lumefantrine. Both components are blood schizontocides. The chemical name of artemether is (3R,5aS,6R,8aS,9R,10S,12R,12aR)-10-methoxy-3,6,9-trimethyldecahydro-3,12-epoxypyrano[4,3-j]-1,2-benzodioxepine. Artemether is a white, crystalline powder that is freely soluble in acetone, soluble in methanol and ethanol, and practically insoluble in water. It has the empirical formula C16H26O5 with a molecular weight of 298.4 g/mol, and the following structural formula:

The chemical name of lumefantrine is (1RS)-2-(dibutylamino)-1-{(9Z)-2,7-dichloro-9-[(4-chlorophenyl)methylene]-9H-fluorene-4-yl}ethanol. Lumefantrine is a yellow, crystalline powder that is freely soluble in N,N-dimethylformamide, chloroform, and ethyl acetate; soluble in dichloromethane; slightly soluble in ethanol and methanol; and insoluble in water. It has the empirical formula C30H32Cl3NO with a molecular weight of 528.9 g/mol, and the following structural formula:

Coartem Tablets are for oral administration. Each Coartem Tablet contains 20 mg of artemether and 120 mg lumefantrine. The inactive ingredients are colloidal silicon dioxide, croscarmellose sodium, hypromellose, magnesium stearate, microcrystalline cellulose, and polysorbate 80.

12 CLINICAL PHARMACOLOGY

12.1 Mechanism of Action

Coartem Tablets, a fixed dose combination of artemether and lumefantrine in the ratio of 1:6, is an antimalarial agent [see Microbiology (12.4)].

12.3 Pharmacokinetics

Absorption

Following administration of Coartem Tablets to healthy volunteers and patients with malaria, artemether is absorbed with peak plasma concentrations reached about 2 hours after dosing. Absorption of lumefantrine, a highly lipophilic compound, starts after a lag-time of up to 2 hours, with peak plasma concentrations about 6 to 8 hours after administration. The single dose (4 tablets) pharmacokinetic parameters for artemether, DHA, an active antimalarial metabolite of artemether, and lumefantrine in adult Caucasian healthy volunteers are given in Table 3. Multiple dose data after the 6-dose regimen of Coartem Tablets in adult malaria patients are given in Table 4.

Table 3: Single Dose Pharmacokinetic Parametersa for Artemether, Dihydroartemisinin, and Lumefantrine Under-Fed Conditions
 | Study 2102 (n = 50) | Study 2104 (n = 48)
Artemether
Cmax (ng/mL) | 60.0 ± 32.5 | 83.8 ± 59.7
Tmax (h) | 1.50 | 2.00
AUClast (ng·h/mL) | 146 ± 72.2 | 259 ± 150
t½ (h) | 1.6 ± 0.7 | 2.2 ± 1.9
DHA
Cmax (ng/mL) | 104 ± 35.3 | 90.4 ± 48.9
Tmax (h) | 1.76 | 2.00
AUClast (ng·h/mL) | 284 ± 83.8 | 285 ± 98.0
t½ (h) | 1.6 ± 0.6 | 2.2 ± 1.5
Lumefantrine
Cmax (µg/mL) | 7.38 ± 3.19 | 9.80 ± 4.20
Tmax (h) | 6.01 | 8.00
AUClast (µg·h/mL) | 158 ± 70.1 | 243 ± 117
t½ (h) | 101 ± 35.6 | 119 ± 51.0
Abbreviations: DHA, dihydroartemisinin; SD, standard deviation; AUC, area under the curve.
aMean ± SD Cmax, AUClast, t½ and Median Tmax.

Food enhances the absorption of both artemether and lumefantrine. In healthy volunteers, the relative bioavailability of artemether was increased between 2- to 3-fold, and that of lumefantrine 16-fold when Coartem Tablets were taken after a high-fat meal compared under fasted conditions. Patients should be encouraged to take Coartem Tablets with a meal as soon as food can be tolerated [see Dosage and Administration (2.1)].

Distribution

Artemether and lumefantrine are both highly bound to human serum proteins in vitro (95.4% and 99.7%, respectively). Dihydroartemisinin (DHA) is also bound to human serum proteins (47% to 76%). Protein binding to human plasma proteins is linear.

Biotransformation

In human liver microsomes and recombinant CYP450 enzymes, the metabolism of artemether was catalyzed predominantly by CYP3A4/5. Dihydroartemisinin (DHA) is an active metabolite of artemether. The metabolism of artemether was also catalyzed to a lesser extent by CYP2B6, CYP2C9 and CYP2C19. In vitro studies with artemether at therapeutic concentrations revealed no significant inhibition of the metabolic activities of CYP1A2, CYP2A6, CYP2C9, CYP2C19, CYP2D6, CYP2E1, CYP3A4/5, and CYP4A9/11. In vitro studies with artemether, DHA, and lumefantrine at therapeutic concentrations revealed no significant induction of the metabolic activities of CYP1A1, CYP1A2, CYP2B6, CYP2C8, CYP2C9, CYP2C19, CYP3A4, or CYP3A5.

During repeated administration of Coartem Tablets, systemic exposure of artemether decreased significantly, while concentrations of DHA increased, although not to a statistically significant degree. The artemether/DHA area under the curve (AUC) ratio is 1.2 after a single dose and 0.3 after 6 doses given over 3 days. This suggests that there was induction of enzymes responsible for the metabolism of artemether.

In human liver microsomes and in recombinant CYP450 enzymes, lumefantrine was metabolized mainly by CYP3A4 to desbutyl-lumefantrine. The systemic exposure to the metabolite desbutyl-lumefantrine was less than 1% of the exposure to the parent compound. In vitro, lumefantrine significantly inhibits the activity of CYP2D6 at therapeutic plasma concentrations.

Caution is recommended when combining Coartem Tablets with substrates, inhibitors, or inducers of CYP3A4, especially antiretroviral drugs and those that prolong the QT interval (e.g., macrolide antibiotics, pimozide) [see Contraindications (4), Warnings and Precautions (5.1, 5.2, 5.3), and Drug Interactions (7)].

Coadministration of Coartem Tablets with CYP2D6 substrates may result in increased plasma concentrations of the CYP2D6 substrate and increase the risk of adverse reactions. In addition, many of the drugs metabolized by CYP2D6 can prolong the QT interval and should not be administered with Coartem Tablets due to the potential additive effect on the QT interval (e.g., flecainide, imipramine, amitriptyline, clomipramine) [see Warnings and Precautions (5.1, 5.4) and Drug Interactions (7.6)].

Elimination

Artemether and DHA are cleared from plasma with an elimination half-life of about 2 hours. Lumefantrine is eliminated more slowly, with an elimination half-life of 3 to 6 days in healthy volunteers and in patients with falciparum malaria. Demographic characteristics such as sex and weight appear to have no clinically relevant effects on the pharmacokinetics of artemether and lumefantrine.

In 16 healthy volunteers, neither lumefantrine nor artemether was found in the urine after administration of Coartem Tablets, and urinary excretion of DHA amounted to less than 0.01% of the artemether dose.

Specific Populations

Hepatic and Renal Impairment

No specific pharmacokinetic studies have been performed in patients with either hepatic or renal impairment. There is no significant renal excretion of lumefantrine, artemether, and DHA in healthy volunteers and while clinical experience in this population is limited, no dose adjustment in renal impairment is recommended [see Dosage and Administration (2.4)].

Pediatric Patients

The PK of artemether, DHA, and lumefantrine were obtained in 2 pediatric studies by sparse sampling using a population-based approach. PK estimates derived from a composite plasma concentration profile for artemether, DHA, and lumefantrine are provided in Table 4.

Systemic exposure to artemether, DHA, and lumefantrine, when dosed on an mg/kg body weight basis in pediatric patients (greater than or equal to 5 to less than 35 kg body weight), is comparable to that of the recommended dosing regimen in adult patients.

Table 4: Summary of Pharmacokinetic Parameters for Lumefantrine, Artemether, and DHA in Pediatric and Adult Patients With Malaria Following Administration of a 6-dose Regimen of Coartem Tablets
 | Adults^1 | Pediatric Patients (body weight, kg)^2
Drug |  | 5 to < 15 | 15 to < 25 | 25 to < 35
Lumefantrine
Mean Cmax, range (mcg/mL) | 5.60-9.0 | 4.71–12.6 |  | Not Available
Mean AUClast, range (mcg·h/mL) | 410-561 | 372–699 |  | Not Available
Artemether
Mean Cmax ± SD (ng/mL) | 186 ± 125 | 223 ± 309 | 198 ± 179 | 174 ± 145
Dihydroartemisinin
Mean Cmax ± SD (ng/mL) | 101 ± 58 | 54.7 ± 58.9 | 79.8 ± 80.5 | 65.3 ± 23.6
Abbreviations: AUC, area under the curve; DHA, dihydroartemisinin; SD, standard deviation.
^1There are a total of 181 adults for lumefantrine pharmacokinetic parameters and a total of 25 adults for artemether and dihydroartemisinin pharmacokinetic parameters.
^2There are 477 children for the lumefantrine pharmacokinetic parameters; for artemether and dihydroartemisinin pharmacokinetic parameters there are 55, 29, and 8 children
for the 5 to less than 15, 15 to less than 25 and the 25 to less than 35 kg groups, respectively.

Geriatric Patients

No specific pharmacokinetic studies have been performed in patients older than 65 years of age.

Drug Interaction Studies

Rifampin (strong CYP3A4 inducer)

Oral administration of rifampin (600 mg daily), a strong CYP3A4 inducer, with Coartem Tablets (6-dose regimen over 3 days) in 6 HIV-1 and tuberculosis co-infected adults without malaria resulted in significant decreases in exposure, in terms of AUC, to artemether, DHA and lumefantrine by 89%, 85%, and 68%, respectively, when compared to exposure values after Coartem Tablets alone. Concomitant use of strong inducers of CYP3A4 such as rifampin, carbamazepine, phenytoin, and St. John’s wort is contraindicated with Coartem Tablets [see Contraindications (4)].

Ketoconazole (potent CYP3A4 inhibitor)

Concurrent oral administration of ketoconazole (400 mg on day 1 followed by 200 mg on Days 2, 3, 4, and 5) with Coartem Tablets (single-dose of 4 tablets of 20 mg artemether/120 mg lumefantrine per tablet) with a meal led to an increase in exposure, in terms of AUC, of artemether (2.3-fold), DHA (1.5-fold), and lumefantrine (1.6-fold) in 13 healthy subjects. The pharmacokinetics of ketoconazole was not evaluated. Based on this study, dose adjustment of Coartem Tablets is considered unnecessary when administered with ketoconazole or other CYP3A4 inhibitors. However, due to the potential for increased concentrations of lumefantrine, which could lead to QT prolongation, Coartem Tablets should be used cautiously with other drugs that inhibit CYP3A4 (e.g., antiretroviral drugs, macrolide antibiotics, antidepressants, imidazole antifungal agents) [see Warnings and Precautions (5.1, 5.3)].

Antimalarials

The oral administration of mefloquine in 14 healthy volunteers administered as 3 doses of 500 mg, 250 mg, and 250 mg, followed 12 hours later by Coartem Tablets (6 doses of 4 tablets of 20 mg artemether/120 mg lumefantrine per tablet), had no effect on plasma concentrations of artemether or the artemether/DHA ratio. In the same study, there was a 30% reduction in Cmax and 40% reduction in AUC of lumefantrine, possibly due to lower absorption secondary to a mefloquine-induced decrease in bile production.

Intravenous administration of a single dose of quinine (10 mg/kg bodyweight) concurrent with the last dose of a 6-dose regimen of Coartem Tablets had no effect on systemic exposure of DHA, lumefantrine, or quinine in 14 healthy volunteers. Mean AUC of artemether were 46% lower when administered with quinine compared to Coartem Tablets alone. This decrease in artemether exposure is not thought to be clinically significant. However, quinine should be used cautiously in patients following treatment with Coartem Tablets due to the long elimination half-life of lumefantrine and the potential for additive effects on the QT interval; ECG monitoring is advised if use of quinine is medically required [see Warnings and Precautions (5.2)].

Antiretroviral Drugs

The oral administration of lopinavir/ritonavir (400 mg/100 mg twice daily for 26 days) in 10 healthy volunteers coadministered with Coartem Tablets (6-dose regimen over 3 days), resulted in a decrease in systemic exposures, in terms of AUC, to artemether and DHA by approximately 40%, but an increase in exposure to lumefantrine by approximately 2.3-fold. The oral administration of efavirenz (600 mg once daily for 26 days) in 12 healthy volunteers coadministered with Coartem Tablets (6-dose regimen over 3 days), resulted in a decrease in exposures to artemether, DHA, and lumefantrine by approximately 50%, 45%, and 20%, respectively. Exposures to lopinavir/ritonavir and efavirenz were not significantly affected by concomitant use of Coartem Tablets. Coartem Tablets should be used cautiously in patients on antiretroviral drugs such as HIV protease inhibitors and non-nucleoside reverse transcriptase inhibitors because decreased artemether, DHA, and/or lumefantrine concentrations may result in a decrease of antimalarial efficacy of Coartem Tablets, and increased lumefantrine concentrations may cause QT prolongation [see Warnings and Precautions (5.3) and Drug Interactions (7.3)].

Hormonal Contraceptives

No clinical drug-drug interaction studies between Coartem Tablets and hormonal contraceptives have been performed. In vitro studies revealed that the metabolism of ethinyl estradiol and levonorgestrel was not induced by artemether, DHA, or lumefantrine. However, artemether has been reported to weakly induce, in humans, the activity of CYP2C19, CYP2B6, and CYP3A4. Therefore, coadministration of Coartem Tablets may potentially reduce the effectiveness of hormonal contraceptives [see Warnings and Precautions (5.3) and Drug Interactions (7.5)].

12.4 Microbiology

Mechanism of Action

Coartem Tablets, a fixed ratio of 1:6 parts of artemether and lumefantrine, respectively, is an antimalarial agent. Artemether is rapidly metabolized into an active metabolite DHA. The antimalarial activity of artemether and DHA has been attributed to endoperoxide moiety. The exact mechanism by which lumefantrine exerts its antimalarial effect is not well defined. Available data suggest lumefantrine inhibits the formation of β-hematin by forming a complex with hemin. Both artemether and lumefantrine were shown to inhibit nucleic acid and protein synthesis.

Activity In Vitro and In Vivo

Artemether and lumefantrine are active against the erythrocytic stages of P. falciparum.

Drug Resistance

There is a potential for development of resistance to artemether and lumefantrine. Strains of P. falciparum with a moderate decrease in susceptibility to artemether or lumefantrine alone can be selected in vitro or in vivo, but not maintained in the case of artemether. Alterations in some genetic regions of P. falciparum [multidrug resistant 1 (pfmdr1), chloroquine resistance transporter (pfcrt), and kelch 13 (K13)] based on in vitro testing and/or identification of isolates in endemic areas where artemether/lumefantrine treatment was administered, have been reported. The clinical relevance of these findings are not known.

12.6 Effects on the Electrocardiogram

In a healthy adult volunteer parallel-group study including a placebo and moxifloxacin control-group (n = 42 per group), the administration of the 6-dose regimen of Coartem Tablets was associated with prolongation of QTcF (Fridericia). Following administration of a 6-dose regimen of Coartem Tablets consisting of 4 tablets per dose (total of 4 tablets of 80 mg artemether/480 mg lumefantrine) taken with food, the maximum mean change from baseline and placebo adjusted QTcF was 7.5 msec (1-sided 95% upper confidence interval: 11 msec). There was a concentration-dependent increase in QTcF for lumefantrine.

In clinical trials conducted in children, no patient had QTcF greater than 500 msec. Over 5% of patients had an increase in QTcF of over 60 msec.

In clinical trials conducted in adults, QTcF prolongation of greater than 500 msec was reported in 3 (0.3%) patients. Over 6% of adults had a QTcF increase of over 60 msec from baseline.

13 NONCLINICAL TOXICOLOGY

13.1 Carcinogenesis, Mutagenesis, Impairment of Fertility

Carcinogenesis

Carcinogenicity studies were not conducted.

Mutagenesis

No evidence of mutagenicity was detected. The artemether-lumefantrine combination was evaluated using the Salmonella and Escherichia/mammalian-microsome mutagenicity test, the gene mutation test with Chinese hamster cells V79, the cytogenetic test on Chinese hamster cells in vitro, and the rat micronucleus test, in vivo.

Impairment of Fertility

Pregnancy rates were reduced by about one-half in female rats dosed for 2 to 4 weeks with the artemether-lumefantrine combination at 1000 mg/kg (about 9 times the clinical dose based on BSA comparisons). Male rats dosed for 89 to 93 days showed increases in abnormal sperm (87% abnormal) at 30 mg/kg doses (about one-third the clinical dose). Higher doses (about 9 times the MRHD) resulted in increased testes weights, decreased sperm motility, and 100% abnormal sperm cells.

13.2 Animal Toxicology and/or Pharmacology

Neonatal rats (7 to 21 days old) were more sensitive to the toxic effects of artemether (a component of Coartem Tablets) than older juvenile rats or adults. Mortality and severe clinical signs were observed in neonatal rats at doses which were well tolerated in pups above 22 days old.

14 CLINICAL STUDIES

14.1 Treatment of Acute, Uncomplicated P. falciparum Malaria

The efficacy of Coartem Tablets was evaluated for the treatment of acute, uncomplicated malaria caused by P. falciparum in HIV negative patients in 8 clinical studies. Uncomplicated malaria was defined as symptomatic P. falciparum malaria without signs and symptoms of severe malaria or evidence of vital organ dysfunction. Baseline parasite density ranged from 500/mcL to 200,000/mcL (0.01% to 4% parasitemia) in the majority of patients. Studies were conducted in partially immune and non-immune adults and children (greater than or equal to 5 kg body weight) with uncomplicated malaria in China, Thailand, sub-Saharan Africa, Europe, and South America. Patients who had clinical features of severe malaria, severe cardiac, renal, or hepatic impairment were excluded.

The studies include two 4-dose studies assessing the efficacy of the components of the regimen, a study comparing a 4-dose versus a 6-dose regimen, and 5 additional 6-dose regimen studies.

Coartem Tablets were administered at 0, 8, 24, and 48 hours in the 4-dose regimen, and at 0, 8, 24, 36, 48, and 60 hours in the 6-dose regimen. Efficacy endpoints consisted of:

- 28-day cure rate, defined as clearance of asexual parasites (the erythrocytic stage) within 7 days without recrudescence by Day 28
- parasite clearance time (PCT), defined as time from first dose until first total and continued disappearance of asexual parasite which continues for a further 48 hours
- fever clearance time (FCT), defined as time from first dose until the first time body temperature fell below 37.5°C and remained below 37.5°C for at least a further 48 hours (only for patients with temperature greater than 37.5°C at baseline)

The modified intent-to-treat (mITT) population includes all patients with malaria diagnosis confirmation who received at least 1 dose of study drug. Evaluable patients generally are all patients who had a Day 7 and a Day 28 parasitological assessment or experienced treatment failure by Day 28.

Studies 1 and 2: The 2 studies, which assessed the efficacy of Coartem Tablets (4 doses of 4 tablets of 20 mg artemether/120 mg lumefantrine) compared to each component alone, were randomized, double-blind, comparative, single center, conducted in China. The efficacy results (Table 5) support that the combination of artemether and lumefantrine in Coartem Tablets had a significantly higher 28-day cure rate compared to artemether and had a significantly faster PCT and FCT compared to lumefantrine.

Table 5: Clinical Efficacy of Coartem Tablets Versus Components (mITT Population)^1
Study No. Region/patient ages | 28-day cure rate^2 n/N (%) patients | Median FCT^3 [25th, 75th percentile] | Median PCT [25th, 75th percentile]
Study 1 China, ages 13 to 57 years
Coartem Tablets | 50/51 (98.0) | 24 hours [9, 48] | 30 hours [24, 36]
Artemether^4 | 24/52 (46.2) | 21 hours [12, 30] | 30 hours [24, 33]
Lumefantrine^5 | 47/52 (90.4) | 60 hours [36, 78] | 54 hours [45, 66]
Study 2 China, ages 12 to 65 years
Coartem Tablets | 50/52 (96.2) | 21 hours [6, 33] | 30 hours [24, 36]
Lumefantrine^6 | 45/51 (88.2) | 36 hours [12, 60] | 48 hours [42, 60]
Abbreviations: FCT, fever clearance time; mITT, modified intent-to-treat; PCT, parasite clearance time.
^1In mITT analysis, patients whose status was uncertain were classified as treatment failures.
^2Efficacy cure rate based on blood smear microscopy.
^3For patients who had a body temperature greater than 37.5°C at baseline only.
^495% Confidence Interval (Coartem Tablets–artemether) on 28-day cure rate: 37.8%, 66.0%.
^5P-value comparing Coartem Tablets to lumefantrine on PCT and FCT: < 0.001.
^6P-value comparing Coartem Tablets to lumefantrine on PCT: < 0.001 and on FCT: < 0.05.

Results of 4-dose studies conducted in areas with high resistance such as Thailand during 1995-96 showed lower efficacy results than the above studies. Therefore, Study 3 was conducted.

Study 3: Study 3 was a randomized, double-blind, 2-center study conducted in Thailand in adults and children (aged greater than or equal to 2 years), which compared the 4-dose regimen (administered over 48 hours) of Coartem Tablets to a 6-dose regimen (administered over 60 hours). Twenty-eight day cure rate in mITT subjects was 81% (96/118) for the Coartem Tablets 6-dose arm as compared to 71% (85/120) in the 4-dose arm.

Studies 4, 5, 6, 7, and 8: In these studies, Coartem Tablets were administered as the 6-dose regimen.

In study 4, a total of 150 adults and children aged greater than or equal to 2 years received Coartem Tablets. In study 5, a total 164 adults and children greater than or equal to 12 years received Coartem Tablets. Both studies were conducted in Thailand.

Study 6 was a study of 165 non-immune adults residing in regions non-endemic for malaria (Europe and Colombia) who contracted acute uncomplicated P. falciparum malaria when traveling in endemic regions.

Study 7 was conducted in Africa in 310 infants and children aged 2 months to 9 years, weighing 5 kg to 25 kg, with an axillary temperature greater than or equal to 37.5ºC.

Study 8 was conducted in Africa in 452 infants and children, aged 3 months to 12 years, weighing 5 kg to less than 35 kg, with fever (greater than or equal to 37.5°C axillary or greater than or equal to 38°C rectally) or history of fever in the preceding 24 hours.

Results of 28-day cure rate, median PCT, and FCT for Studies 3 to 8 are reported in Table 6.

Table 6: Clinical Efficacy of 6-dose Regimen of Coartem Tablets
Study No. Region/ages | 28-day cure rate^1 n/N (%) Patients |  | Median FCT^2 [25th, 75th percentile] | Median PCT [25th, 75th percentile]
 | mITT^3 | Evaluable
Study 3 Thailand, ages 3–62 years | 96/118 (81.4) | 93/96 (96.9) | 35 hours [20, 46] | 44 hours [22, 47]
Early failure^4 | 0 | 0
Late failure^5 | 4 (3.4) | 3 (3.1)
Lost to follow-up | 18 (15.3)
Other^6 | 0
Study 4 Thailand, ages 2–63 years | 130/149 (87.2) | 130/134 (97.0) | 22 hours [19, 44] | NA
Early failure^4 | 0 | 0
Late failure^5 | 4 (2.7) | 4 (3.0)
Lost to follow-up | 13 (8.7)
Other^6 | 2 (1.3)
Study 5 Thailand, ages 12–71 years | 148/164 (90.2) | 148/155 (95.5) | 29 hours [8, 51] | 29 hours [18, 40]
Early failure^4 | 0 | 0
Late failure^5 | 7 (4.3) | 7 (4.5)
Lost to follow-up | 9 (5.5)
Other^6 | 0
Study 6 Europe/Columbia, ages 16–66 years | 120/162 (74.1) | 119/124 (96.0) | 37 hours [18, 44] | 42 hours [34, 63]
Early failure^4 | 6 (3.7) | 1 (0.8)
Late failure^5 | 3 (1.9) | 3 (2.4)
Lost to follow-up | 17 (10.5)
Other^6 | 16 (9.9) | 1 (0.8)
Study 7 Africa, ages 2 months–9 years | 268/310 (86.5) | 267/300 (89.0) | 8 hours [8, 24] | 24 hours [24, 36]
Early failure^4 | 2 (0.6) | 0
Late failure^5 | 34 (11.0) | 33 (11.0)
Lost to follow-up | 2 (0.6)
Other^6 | 4 (1.3)
Study 8 Africa, ages 3 months–12 years | 374/452 (82.7) | 370/419 (88.3) | 8 hours [8, 23] | 35 hours [24, 36]
Early failure^4 | 13 (2.9) | 0
Late failure^5 | 49 (10.8) | 49 (11.7)
Lost to follow-up | 6 (1.3)
Other^6 | 10 (2.2)
Abbreviations: FCT, fever clearance time; mITT, modified intent-to-treat; PCT, parasite clearance time; NA, not applicable.
^1Efficacy cure rate based on blood smear microscopy.
^2For patients who had a body temperature greater than 37.5°C at baseline only.
^3In mITT analysis, patients whose status was uncertain were classified as treatment failures.
^4Early failures were usually defined as patients withdrawn for unsatisfactory therapeutic effect within the first 7 days or because they received another antimalarial medication within the first 7 days.
^5Late failures were defined as patients achieving parasite clearance within 7 days but having parasite reappearance including recrudescence or new infection during the 28-day follow-up period.
^6Other includes withdrawn due to protocol violation or non-compliance, received additional medication after day 7, withdrew consent, missing day 7 or 28 assessment.

In all studies, patients’ signs and symptoms of malaria resolved when parasites were cleared.

In studies conducted in areas with high transmission rates, such as Africa, reappearance of P. falciparum parasites may be due to recrudescence or a new infection.

The efficacy by body weight category for studies 7 and 8 is summarized in Table 7.

Table 7: Clinical Efficacy by Weight for Pediatric Studies
Study No. Age category | Coartem Tablets 6-dose Regimen
 | mITT Population^1 |  | Evaluable Population
 | Median PCT [25 th, 75 th percentile] | 28-day cure rate^2 n/N (%) patients | 28-day cure rate^2 n/N (%) patients
Study 7
5 to < 10 kg | 24 [24, 36] | 133/154 (86.4) | 133/149 (89.3)
10 to < 15 kg | 35 [24, 36] | 94/110 (85.5) | 94/107 (87.9)
15 to 25 kg | 24 [24, 36] | 41/46 (89.1) | 40/44 (90.9)
Study 8^3
5 to < 10 kg | 36 [24, 36] | 61/83 (73.5) | 61/69 (88.4)
10 to < 15 kg | 35 [24, 36] | 160/190 (84.2) | 157/179 (87.7)
15 to < 25 kg | 35 [24, 36] | 123/145 (84.8) | 123/140 (87.9)
25 to < 35 kg | 26 [24, 36] | 30/34 (88.2) | 29/31 (93.5)
Abbreviations: mITT, modified intent-to-treat; PCT, parasite clearance time.
^1In mITT analysis, patients whose status was uncertain were classified as treatment failures.
^2Efficacy cure rate based on blood smear microscopy.
^3Coartem Tablets administered as crushed tablets.

The efficacy of Coartem Tablets for the treatment P. falciparum infections mixed with P. vivax was assessed in a small number of patients. Coartem Tablets are only active against the erythrocytic phase of P. vivax malaria. Of the 43 patients with mixed infections at baseline, all cleared their parasitemia within 48 hours. However, parasite relapse occurred commonly (14/43; 33%). Relapsing malaria caused by P. vivax requires additional treatment with other antimalarial agents to achieve radical cure i.e., eradicate any hypnozoite forms that may remain dormant in the liver.

16 HOW SUPPLIED/STORAGE AND HANDLING

Coartem (artemether/lumefantrine) Tablets

20 mg/120 mg Tablets - yellow, round flat tablets with beveled edges and scored on one side. Tablets are imprinted with “N/C” on one side and “CG” on the other.

Bottle of 24 NDC 0078-0568-45

Store at 20ºC to 25ºC (68ºF to 77ºF); excursions permitted to 15ºC to 30ºC (59ºF to 86ºF) [see USP Controlled Room Temperature].

Dispense in tight container (USP).

17 PATIENT COUNSELING INFORMATION

Advise patients to read the FDA-Approved Patient Labeling (Patient Information).

Administration Instructions

Instruct patients to take Coartem Tablets with food. Patients who do not have an adequate intake of food are at risk for recrudescence of malaria [see Dosage and Administration (2.1)].

Hypersensitivity

Patients with known hypersensitivity to artemether, lumefantrine, or to any of the excipients should not receive Coartem Tablets [see Contraindications (4)].

Prolongation of the QT Interval

- Instruct patients to inform their physician of any personal or family history of QT prolongation or proarrhythmic conditions such as hypokalemia, bradycardia, or recent myocardial ischemia [see Warnings and Precautions (5.1)].
- Instruct patients to inform their physician if they are taking any other medications that prolong the QT interval, such as Class IA (quinidine, procainamide, disopyramide), or Class III (amiodarone, sotalol) antiarrhythmic agents; antipsychotics (pimozide, ziprasidone); antidepressants; certain antibiotics (macrolide antibiotics, fluoroquinolone antibiotics, imidazole, and triazole antifungal agents) [see Warnings and Precautions (5.1)].
- Instruct patients to notify their physicians if they have any symptoms of prolongation of the QT interval, including prolonged heart palpitations or a loss of consciousness [see Warnings and Precautions (5.1)].

Drug Interactions With CYP2D6

Instruct patients to avoid medications that are metabolized by the cytochrome enzyme CYP2D6 while receiving Coartem Tablets since these drugs also have cardiac effects (e.g., flecainide, imipramine, amitriptyline, clomipramine) [see Warnings and Precautions (5.4)].

Contraception

Advise patients that use of Coartem may reduce the efficacy of hormonal contraceptives. Advise patients using hormonal contraceptive to use an alternative non-hormonal contraceptive method or add a barrier method of contraception during treatment with Coartem [see Drug Interactions (7.5) and Use in Specific Populations (8.3)].

Use of QT Prolonging Drugs and Other Antimalarials

Halofantrine and Coartem Tablets should not be administered within 1 month of each other due to potential additive effects on the QT interval. Antimalarials should not be given concomitantly with Coartem Tablets, unless there is no other treatment option, due to limited safety data [see Warnings and Precautions (5.2)].

Sequential Use of Quinine

QT prolonging drugs, including quinine and quinidine, should be used cautiously following Coartem Tablets due to the long elimination half-life of lumefantrine and the potential for additive effects on the QT interval. ECG monitoring is advised if use of drugs that prolong the QT interval is medically required [see Drug Interactions (7.7)].

Prior Use of Mefloquine

Closely monitor food intake in patients who received mefloquine immediately prior to treatment with Coartem Tablets [see Drug Interactions (7.4)].

Drug Interactions With CYP3A4

Use Coartem Tablets cautiously in patients receiving other drugs that are substrates, inhibitors or inducers of CYP3A4, including grapefruit juice, especially those that prolong the QT interval or are antiretroviral drugs. Coadministration of strong inducers of CYP3A4 such as rifampin, carbamazepine, phenytoin, and St. John’s wort is contraindicated with Coartem Tablets [see Warnings and Precautions (5.3)].

Hypersensitivity Reactions

Inform patients that Coartem Tablets can cause hypersensitivity reactions. Instruct patients to discontinue the drug at the first sign of a skin rash, hives or other skin reactions, a rapid heartbeat, difficulty in swallowing or breathing, any swelling suggesting angioedema (e.g., swelling of the lips, tongue, face, tightness of the throat, hoarseness), or other symptoms of an allergic reaction [see Contraindications (4)].

T2019-88

Patient Information
Coartem® (co-AR-tem)
(artemether and lumefantrine)
tablets, for oral use

Read this Patient Information leaflet before you start taking Coartem. There may be new information. This information does not take the place of talking to your healthcare provider about your medical condition or your treatment.

What is Coartem?
Coartem is a prescription medicine used to treat uncomplicated malaria caused by the parasite Plasmodium falciparum (P. falciparum) in people 2 months of age and older who weigh at least 11 pounds (5 kg).

Coartem is not approved to:

- Treat severe or complicated P. falciparum malaria
- Prevent malaria

It is not known if Coartem is safe and effective in children who weigh less than 11 pounds (5 kg).

Who should not take Coartem?
Do not take Coartem if you:

- are allergic to artemether, lumefantrine, or any of the ingredients in Coartem. See the end of this Patient Information leaflet for a complete list of ingredients in Coartem. Symptoms of a serious allergic reaction with Coartem can include: rash, hives, fast heartbeat, trouble swallowing or breathing, swelling of lips, tongue, face, tightness of the throat, or trouble speaking. If you have any of these symptoms of a serious allergic reaction while taking Coartem, stop taking Coartem and get emergency medical help right away.
- are taking rifampin (medicine used to treat leprosy or tuberculosis), carbamazepine or phenytoin (medicines used to treat epilepsy), or St. John’s wort (Hypericum perforatum, a medicinal plant or extract of this medicinal plant).

What should I tell my healthcare provider before taking Coartem?
Before taking Coartem, tell your healthcare provider about all of your medical conditions, including if you:

- have heart disease or a family history of heart problems or heart disease.
- have liver or kidney problems.
- have recently taken other medicines used to treat malaria.
- are pregnant or plan to become pregnant. Treatment of malaria is important because it can be a serious disease for a pregnant woman and her unborn baby.
- are taking hormonal contraceptives (such as birth control pills). Coartem may affect how well hormonal contraceptives work and may cause them to not work as well. Females who are able to become pregnant should use another effective non-hormonal form of birth control or an additional barrier method of birth control (such as male condoms) during treatment with Coartem. Talk with your healthcare provider if you have questions about birth control methods that may be right for you during this time.
- are breastfeeding or plan to breastfeed. It is not known if Coartem passes into your breast milk. Talk to your healthcare provider about the best way to feed your baby while taking Coartem.

Tell your healthcare provider about all the medicines you take, including prescription and over-the-counter medicines, vitamins, and herbal supplements. Coartem and other medicines may affect each other causing side effects. Coartem may affect the way other medicines work and other medicines may affect how Coartem works.

Especially tell your healthcare provider if you take:

- any other medicines to treat or prevent malaria
- medicines for your heart
- antipsychotic medicines
- antidepressants
- medicines for seizures or trigeminal neuralgia (facial nerve pain)
- antibiotics (including medicines to treat tuberculosis)
- antifungal medicines (such as itraconazole, ketoconazole, and fluconazole)
- medicines to treat HIV-infection
- hormonal methods of birth control. See “What should I tell my healthcare provider before taking Coartem?”

Ask your healthcare provider if you are not sure if your medicine is listed above. Know the medicines you take. Keep a list of your medicines with you and show it to your healthcare provider and pharmacist when you get a new medicine.

How should I take Coartem?

- Take Coartem exactly as prescribed.
- If you weigh 77 pounds (35 kg) or more, 1 dose of Coartem is 4 tablets. A full course of treatment is 6 doses (24 tablets) of Coartem taken over 3 days:
  - Day 1: take 1 dose, then 8 hours later take 1 dose
  - Day 2: take 1 dose in the morning, 1 dose in the evening
  - Day 3: take 1 dose in the morning, 1 dose in the evening
    Important: Take the full course of treatment with Coartem for all 3 days even if you are feeling better.
- If you weigh less than 77 pounds (35 kg), your healthcare provider will tell you how many tablets to take for each dose.
- Each dose of Coartem should be taken with food or drink, such as milk, infant formula, pudding, porridge, or broth. It is important for you to eat as soon as you can so that your malaria will go away and not get worse.
- Do not drink grapefruit juice while you take Coartem. Drinking grapefruit juice during treatment with Coartem can cause you to have too much medicine in your blood.
- If you are not able to swallow Coartem tablets, Coartem may be crushed and mixed with 1 to 2 teaspoons of water in a clean container. If any medicine remains, you can add more water to the container and drink right away.
- If you vomit within 1 to 2 hours after taking Coartem, you should take another dose of Coartem. If you vomit the second dose, tell your healthcare provider. A different medicine may need to be prescribed for you.

Tell your healthcare provider right away if:

- your malaria does not get better or you get flu-like symptoms such as chills, fever, muscle pains, or headaches again after you finish treatment with Coartem
- you vomit any doses of Coartem
- you are not able to eat
- you have any change in the way your heart beats or a loss of consciousness (fainting)

What are the possible side effects of Coartem?
Coartem can cause serious side effects, including:

- A heart problem called QT prolongation that can cause an abnormal heartbeat can happen in people who take Coartem. The chance of this happening is higher in people with a family history of prolonged QT interval, low potassium (hypokalemia) or low magnesium (hypomagnesemia), and in people who take certain medicines including medicine to control heartbeats.

The most common side effects of Coartem in adults include:

- headache
- not wanting to eat
- dizziness
- fever

- weakness or lack of energy
- joint pain
- muscle pain, tenderness and weakness

The most common side effects of Coartem in children include:

- fever
- cough
- vomiting

- not wanting to eat
- headache

These are not all the possible side effects of Coartem. For more information, ask your doctor or pharmacist. Call your doctor for medical advice about side effects. You may report side effects to FDA at 1-800-FDA-1088.

How should I store Coartem?

- Store Coartem at room temperature between 68°F to 77°F (20°C to 25°C).
- Store Coartem in the original container and keep the container tightly closed.

Keep Coartem and all medicines out of the reach of children.

General information about the safe and effective use of Coartem.
Medicines are sometimes prescribed for purposes other than those listed in a Patient Information leaflet. Do not use Coartem for a condition for which it was not prescribed. Do not give Coartem to other people, even if they have the same symptoms that you have. It may harm them.
This Patient Information leaflet summarizes the most important information about Coartem. If you would like more information about Coartem talk with your healthcare provider. You can ask your healthcare provider or pharmacist for information about Coartem that is written for health professionals.

What are the ingredients in Coartem?
Active ingredients: artemether, lumefantrine
Inactive ingredients: colloidal silicon dioxide, croscarmellose sodium, hypromellose, magnesium stearate, microcrystalline cellulose, and polysorbate 80
Distributed by:
Novartis Pharmaceuticals Corporation
East Hanover, New Jersey 07936
© Novartis
T2024-76
For more information about Coartem, call 1-888-669-6682.

This Patient Information has been approved by the U.S. Food and Drug Administration.

Revised: November 2024

PRINCIPAL DISPLAY PANEL

NDC 0078-0568-45 Rx only

Coartem®
(artemether/lumefantrine)
Tablets

20 mg/120 mg per tablet

24 Tablets

NOVARTIS